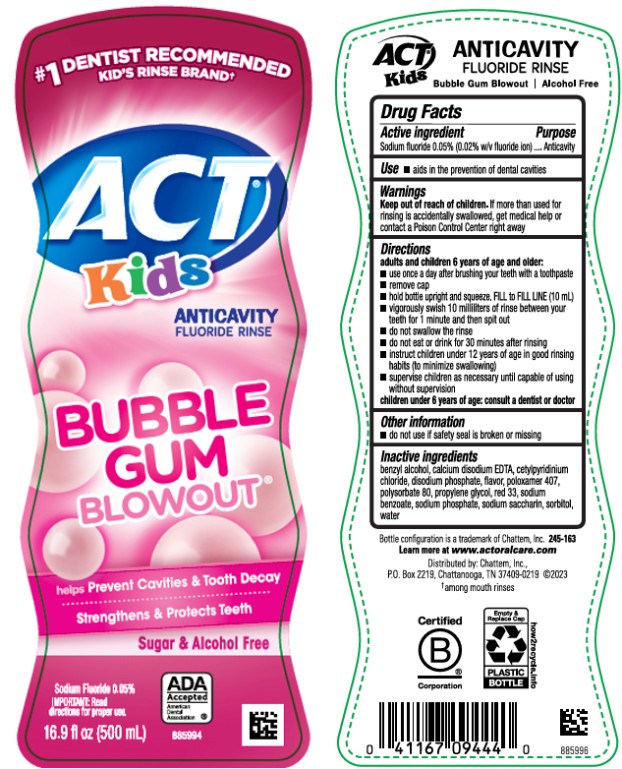 DRUG LABEL: ACT Anticavity Fluoride Kids Bubblegum
NDC: 41167-0944 | Form: RINSE
Manufacturer: Chattem, Inc.
Category: otc | Type: HUMAN OTC DRUG LABEL
Date: 20260112

ACTIVE INGREDIENTS: SODIUM FLUORIDE 0.2 mg/1 mL
INACTIVE INGREDIENTS: BENZYL ALCOHOL; EDETATE CALCIUM DISODIUM ANHYDROUS; CETYLPYRIDINIUM CHLORIDE; POLOXAMER 407; POLYSORBATE 80; PROPYLENE GLYCOL; D&C RED NO. 33; SODIUM BENZOATE; SODIUM PHOSPHATE; SACCHARIN SODIUM; SORBITOL; WATER

ACT Anticavity Fluoride Rinse Kids Bubblegum

Drug Facts

Active Ingredient

Sodium fluoride 0.05% (0.02% w/v fluoride ion)

Purpose

Anticavity

Use

- aids in the prevention of dental cavities

Warnings

Keep out of reach of children.

If more than used for rinsing is accidentally swallowed, get medical help or contact a Poison Control Center right away.

Directions

adults and children 6 years of age and older:

- use once a day after brushing your teeth with a toothpaste
- remove cap
- hold bottle upright and squeeze. Fill to FILL LINE
- pour out. Only the correct 10 milliliters dose will pour out.
- vigorously swish 10 milliliters of rinse between your teeth for 1 minute and then spit out
- do not swallow the rinse
- do not eat or drink for 30 minutes after rinsing
- instruct children under 12 years of age in good rinsing habits (to minimize swallowing)
- supervise children as necessary until capable of using without supervision

children under 6 years of age: consult a dentist or doctor

Other Information

- do not use if safety seal is broken or missing

Inactive ingredients

benzyl alcohol, calcium disodium EDTA, cetylpyridinium chloride, disodium phosphate, flavor, poloxamer 407, polysorbate 80, propylene glycol, red 33, sodium benzoate, sodium phosphate, sodium saccharin, sorbitol, water (245-163)

Learn more at www.actfluoride.com

PRINCIPAL DISPLAY PANEL

#1 DENTIST RECOMMENDED
KID’S RINSE BRAND
ACT Kids
ANTICAVITY
FLUORIDE RINSE
BUBBLE GUM BLOWOUT
16.9 fl oz (500 mL)